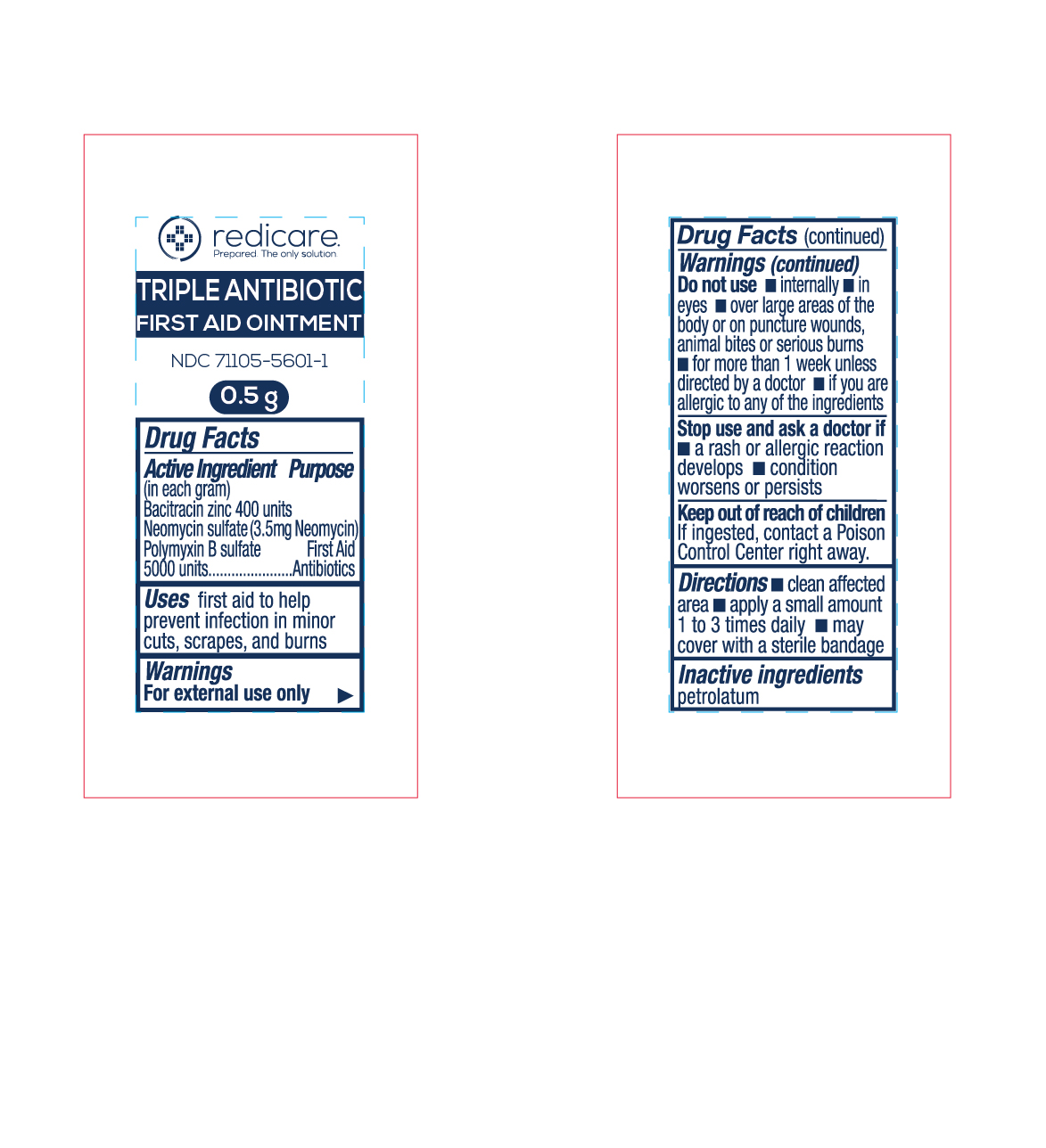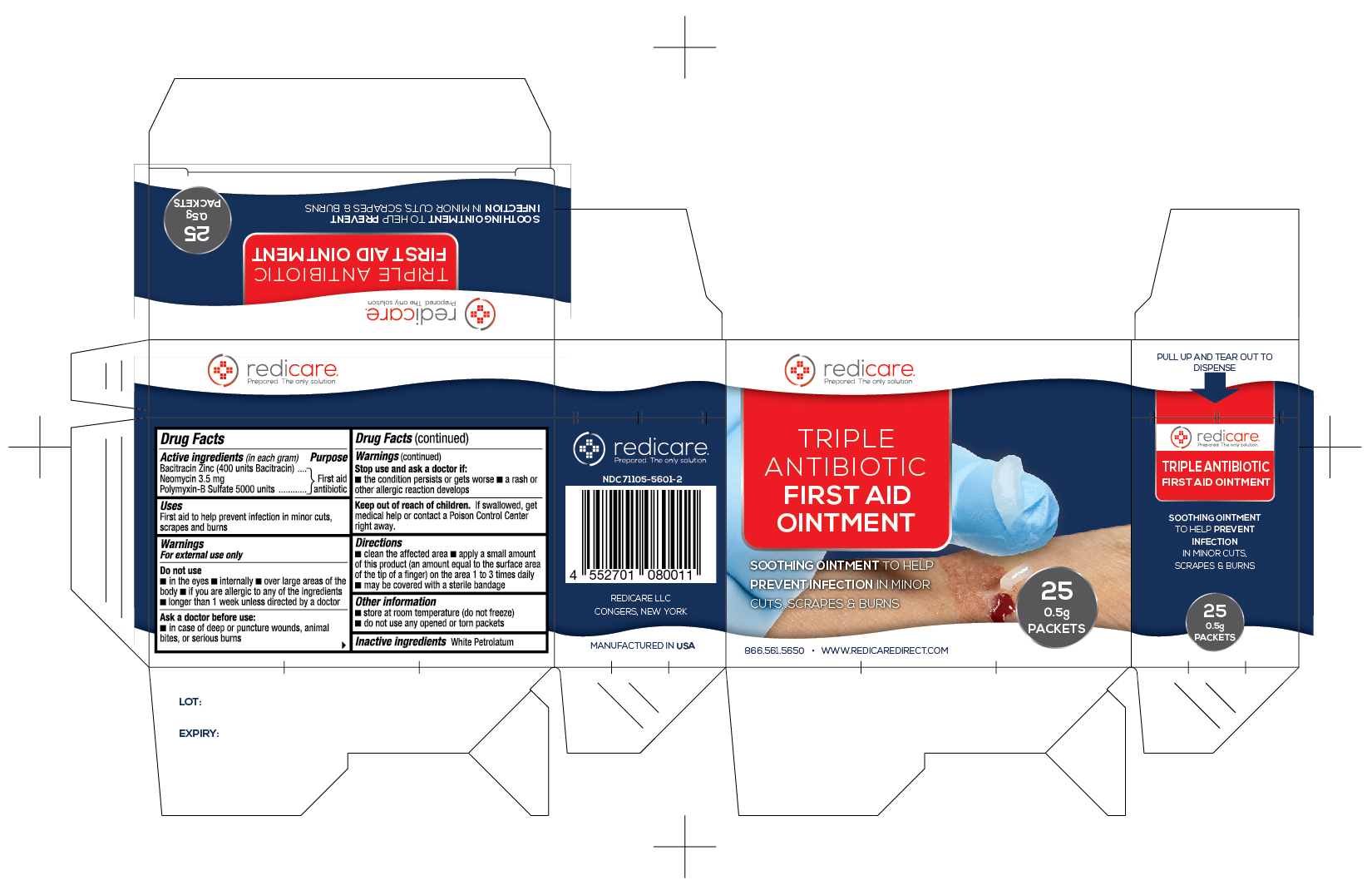 DRUG LABEL: Redicare Triple Antibiotic First Aid
NDC: 71105-560 | Form: OINTMENT
Manufacturer: Redicare LLC
Category: otc | Type: HUMAN OTC DRUG LABEL
Date: 20250305

ACTIVE INGREDIENTS: BACITRACIN ZINC 400 [USP'U]/1 g; NEOMYCIN SULFATE 3.5 mg/1 g; POLYMYXIN B SULFATE 5000 [USP'U]/1 g
INACTIVE INGREDIENTS: PETROLATUM

Triple Antibiotic

Active Ingredient

- Bacitracin Zinc 400 units
- Neomycin sulfate (3.5 mg Neomycin)
- Polymyxin B Sulfate 5000 units

Purpose

First Aid Antibiotics

Uses

first aid to help prevent infection in minor cuts, scrapes, and burns

Warnings

For external use only

Do not use

- internally
- in eyes
- over large areas of the body or on puncture wounds, animal bites or serious burns
- for more than 1 week unless directed by a doctor
- if you are allergic to any of the ingredients

Stop use and ask a doctor if

- a rash or allergic reation develops
- condition worsens or persists

Keep out of reach of children

If ingested, contact a Poison Control Center right away

Directions

- clean affected area
- apply a small amount 1 to 3 times daily
- may cover with a sterile bandage

Inactive Ingredients

petrolatum